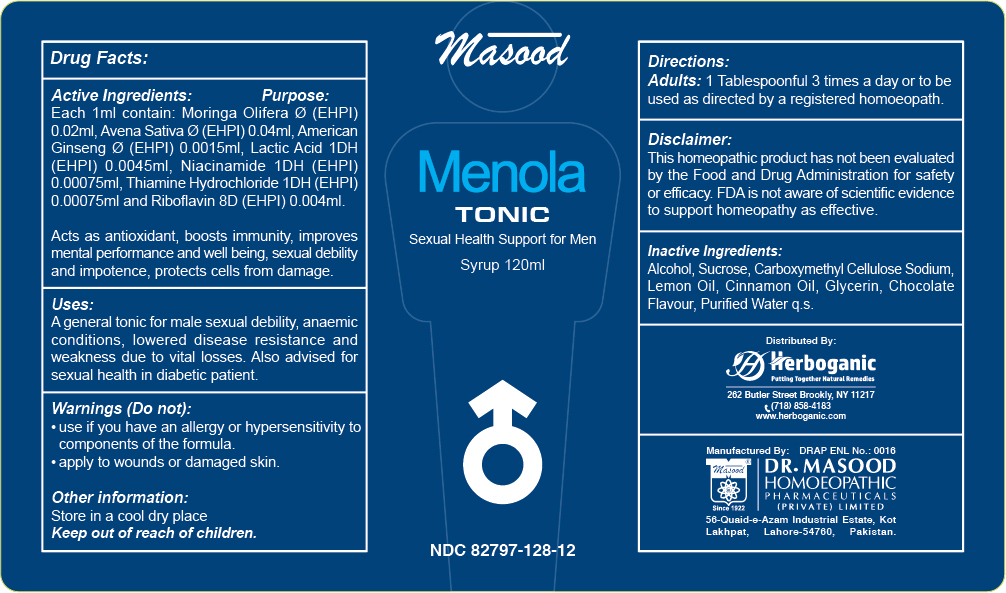 DRUG LABEL: Menola Tonic
NDC: 82797-128 | Form: SYRUP
Manufacturer: Dr. Masood Homeopathic Pharmaceuticals Private Limited
Category: homeopathic | Type: HUMAN OTC DRUG LABEL
Date: 20240702

ACTIVE INGREDIENTS: RIBOFLAVIN 0.48 mg/120 mL; THIAMINE HYDROCHLORIDE 0.09 mg/120 mL; NIACINAMIDE 0.09 mg/120 mL; LACTIC ACID 0.54 mg/120 mL; AMERICAN GINSENG 0.18 mg/120 mL; MORINGA OLEIFERA LEAF 2.4 mg/120 mL; AVENA SATIVA WHOLE 4.8 mg/120 mL
INACTIVE INGREDIENTS: SUCROSE 39 mg/120 mL; CARBOXYMETHYLCELLULOSE SODIUM 0.3 mg/120 mL; ALCOHOL 2.4 mL/120 mL; GLYCERIN 0.9 mL/120 mL; CINNAMON OIL 0.012 mL/120 mL; LEMON OIL 0.024 mL/120 mL

Dosage and Administration

Adults: 1 tablespoonful 3 times a day

Indications and Usage Section

Menola tonic is for male sexual debility and general weakness.
Effective in anemic conditions and lowered disease resistance.
Acts as a tonic for nervous exhaustion.
Also advised during convalescence.

Active Ingredients

- Moringa Olifera
- American Ginseng
- Avena Sativa
- Lactic Acid
- Niacinamide
- Thiamine Hydrochloride
- Riboflavin

Keep out of the reach of children

Keep this and all medicnes out of the reach of children

Purpose

Moringa Olifera Acts as antioxidants, protects cells from damage
American Ginseng Helps boost immune system, improves mental performance and well being

Avena Sativa Acts as a tonic in nervous exhaustion, sexual debility, and impotence.

Lactic Acid used to treat rheumatism and arthritis.

Niacinamide to prevent vitamin B3 deficiency and related conditions such as pellagra
Thiamine Hydrochloride treats tingling and numbness in feet and hands, muscle loss, and poor reflexes
Riboflavin Acts as antioxidant

Warnings

Do not:

use if you have an allergy or hypersensitivity to components of the formula

Other information:

Store in a cool dry place

Inactive Ingredients

Alcohol

Sucrose

Glycerine

Carboxymethyl Cellulose Sodium

Cinnamon Oil

Lemon Oil